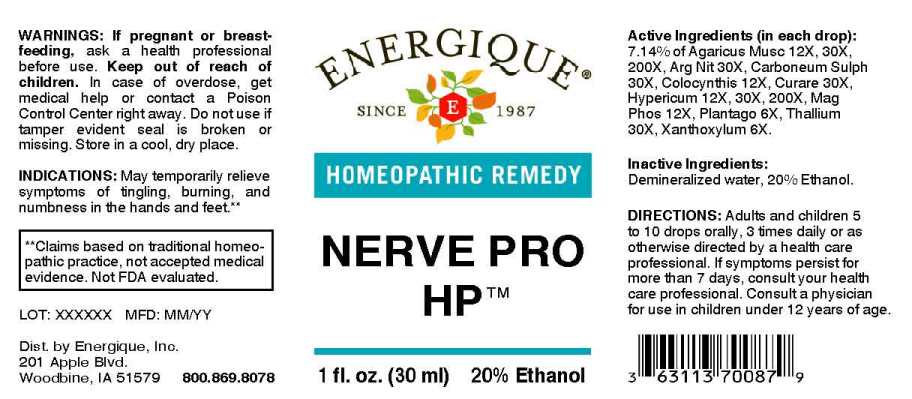 DRUG LABEL: Nerve Pro
NDC: 44911-0495 | Form: LIQUID
Manufacturer: Energique, Inc.
Category: homeopathic | Type: HUMAN OTC DRUG LABEL
Date: 20241029

ACTIVE INGREDIENTS: PLANTAGO MAJOR WHOLE 6 [hp_X]/1 mL; ZANTHOXYLUM AMERICANUM BARK 6 [hp_X]/1 mL; CITRULLUS COLOCYNTHIS FRUIT PULP 12 [hp_X]/1 mL; MAGNESIUM PHOSPHATE, DIBASIC TRIHYDRATE 12 [hp_X]/1 mL; AMANITA MUSCARIA FRUITING BODY 12 [hp_X]/1 mL; HYPERICUM PERFORATUM WHOLE 12 [hp_X]/1 mL; SILVER NITRATE 30 [hp_X]/1 mL; CARBON DISULFIDE 30 [hp_X]/1 mL; TUBOCURARINE CHLORIDE 30 [hp_X]/1 mL; THALLIUM 30 [hp_X]/1 mL
INACTIVE INGREDIENTS: WATER; ALCOHOL

DRUG FACTS:

ACTIVE INGREDIENTS:

(in each drop): 7.14% of Agaricus Muscarius 12X, 30X, 200X, Argentum Nitricum 30X, Carboneum Sulphuratum 30X, Colocynthis 12X, Curare 30X, Hypericum Perforatum 12X, 30X, 200X, Magnesia Phosphorica 12X, Plantago Major 6X, Thallium Metallicum 30X, Xanthoxylum Fraxineum 6X.

INDICATIONS:

May temporarily relieve symptoms of tingling, burning, and numbness in the hands and feet.**

**Claims based on traditional homeopathic practice, not accepted medical evidence. Not FDA evaluated.

WARNINGS:

If pregnant or breastfeeding, ask a health professional before use.

Keep out of reach of children. In case of overdose, get medical help or contact a Poison Control Center right away.

Do not use if tamper evident seal is broken or missing.

Store in a cool, dry place.

Keep out of reach of children. In case of overdose, get medical help or contact a Poison Control Center right away.

DIRECTIONS:

Adults and children 5 to 10 drops orally, 3 times daily or as otherwise directed by a health care professional. If symptoms persist for more than 7 days, consult your health care professional. Consult a physician for use in children under 12 years of age.

INDICATIONS:

May temporarily relieve symptoms of tingling, burning, and dumbness in the hands and feet.**

**Claims based on traditional homeopathic practice, not accepted medical evidence. Not FDA evaluated.

INACTIVE INGREDIENTS:

Demineralized water, 20% Ethanol.

QUESTIONS:

Dist. by Energique, Inc.
201 Apple Blvd.
Woodbine, IA 51579 800.869.8078

PACKAGE LABEL DISPLAY:

ENERGIQUE
SINCE 1987
HOMEOPATHIC REMEDY
NERVE PRO

HP
1 fl. oz. (30 ml)